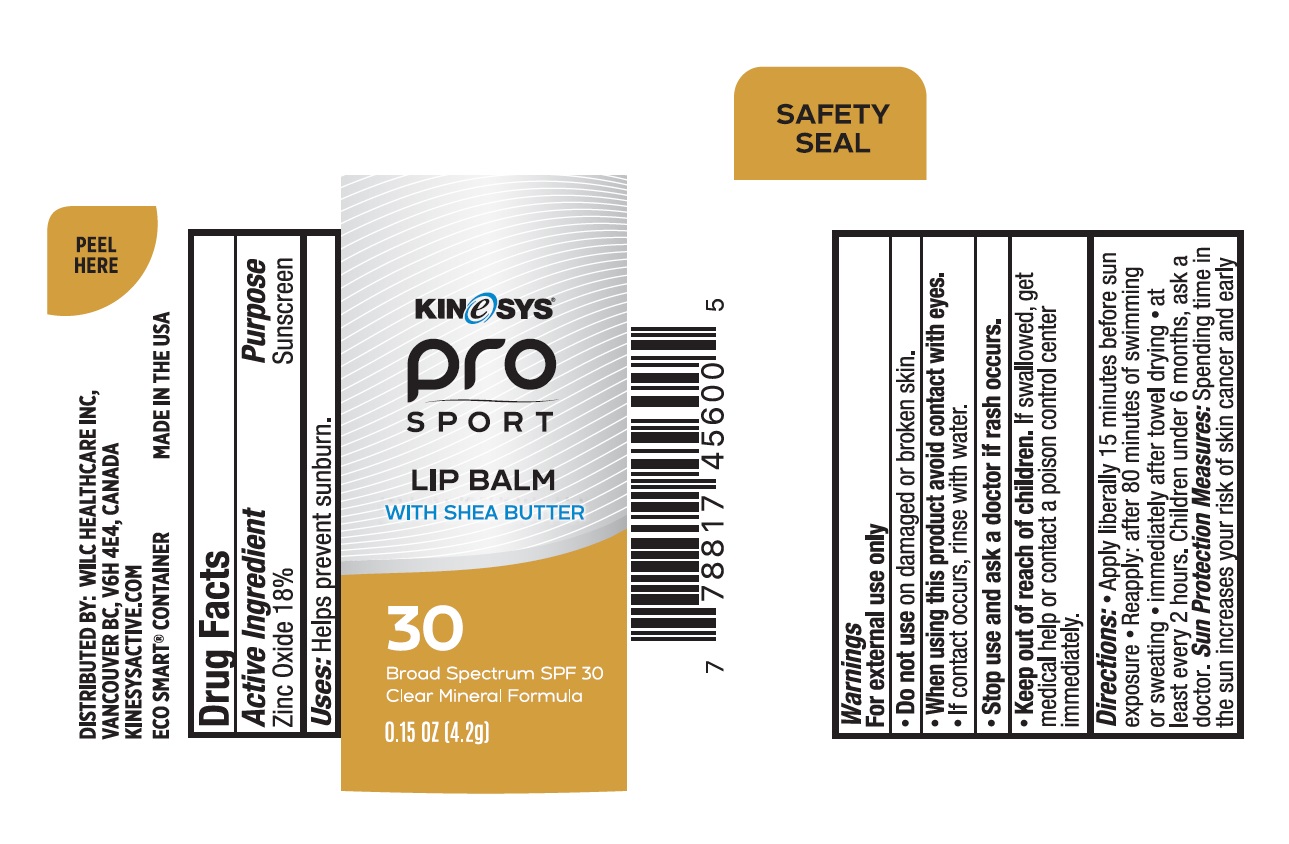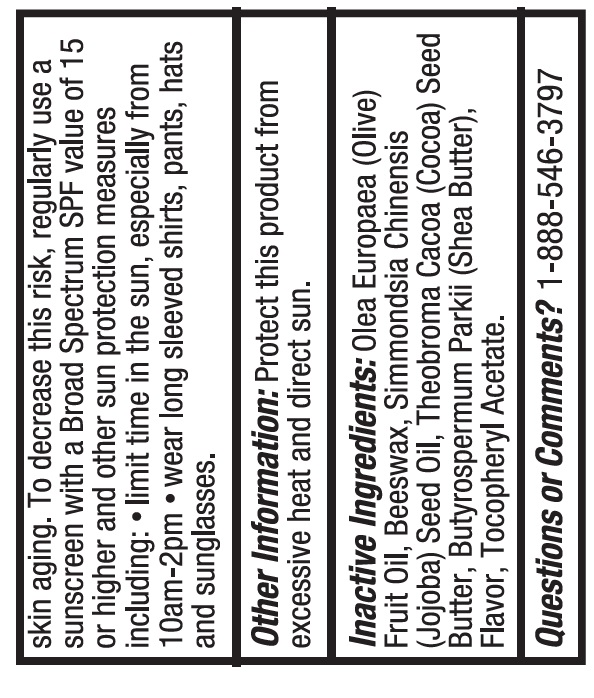 DRUG LABEL: KINeSYS Pro Sport Lip Balm with Shea Butter Broad Spectrum 30
NDC: 61481-3007 | Form: STICK
Manufacturer: Wilc Healthcare Inc
Category: otc | Type: HUMAN OTC DRUG LABEL
Date: 20251010

ACTIVE INGREDIENTS: ZINC OXIDE 18 g/100 g
INACTIVE INGREDIENTS: OLEA EUROPAEA (OLIVE) OIL UNSAPONIFIABLES; WHITE WAX; JOJOBA OIL; COCOA BUTTER; SHEA BUTTER; .ALPHA.-TOCOPHEROL ACETATE

Active Ingredient

Zinc Oxide 18%

Purpose

Sunscreen

Uses

- helps prevent sunburn

Warnings

For external use only
Do not useon damaged or broken skin.
When using this productavoid contact with eyes. If contact occurs, rinse with water.
Stop use and ask a doctor ifrash occurs.
Keep out of reach of children. If swallowed, get medical help or contact a poison control center immediately.

Directions

Apply liberally 15 minutes before sun exposure

Reapply: after 8o minutes of swimming or sweating

- immediately after towel drying
- at least every 2 hours
- Children under 6 months, ask a doctor.

Sun Protection Measures: Spending time in the sun increases your risk of skin cancer and early skin aging. To decrease this risk, regularly use a sunscreen with a Broad Spectrum SPF value of 15 or higher and other sun protection measures including:

- limit time in the sun, especially from 10am-2pm
- wear long sleeved shirts, pants, hats and sunglasses.

Other Information

Protect this product from excessive heat and direact sun

Inactive Ingredients

Olea Europaea (Olive) Oil, Beeswax, Simmondsia Chinensis (Jojoba) Seed Oil, Theobroma Cacoa (Cocoa) Seed Butter, Butyrospermum Parkii (Shea Butter), Flavor, Tocopheryl Acetate

Question or Comments?

1-888-546-3797